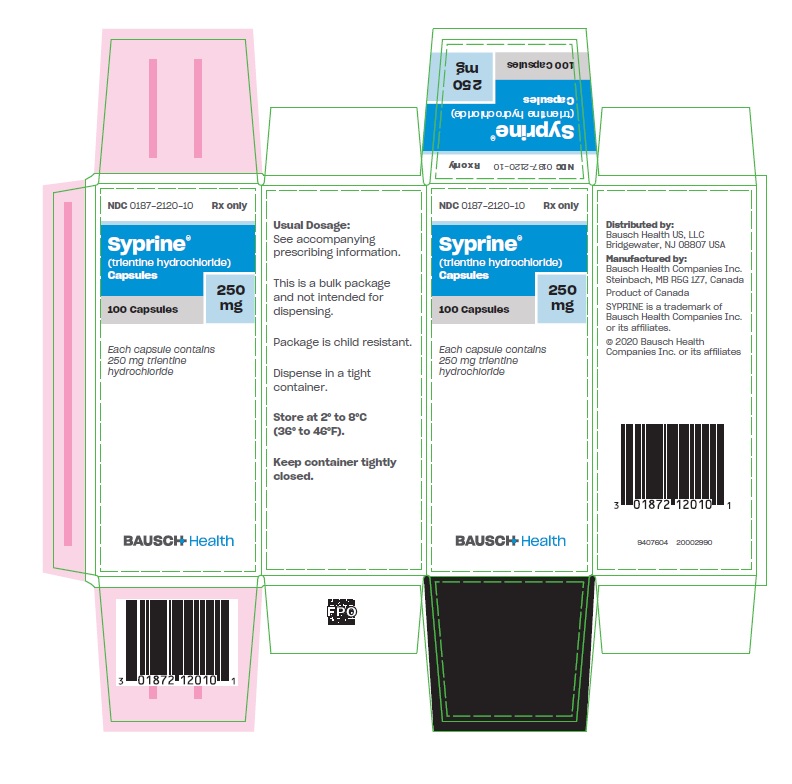 DRUG LABEL: Syprine
NDC: 0187-2120 | Form: CAPSULE
Manufacturer: Bausch Health US LLC
Category: prescription | Type: HUMAN PRESCRIPTION DRUG LABEL
Date: 20200901

ACTIVE INGREDIENTS: trientine hydrochloride 250 mg/1 1
INACTIVE INGREDIENTS: GELATIN, UNSPECIFIED; Stearic Acid; Titanium Dioxide

Syprine®
(trientine hydrochloride)
Capsules

DESCRIPTION

Trientine hydrochloride is N,N'-bis (2-aminoethyl)-1,2-ethanediamine dihydrochloride. It is a white to pale yellow crystalline hygroscopic powder. It is freely soluble in water, soluble in methanol, slightly soluble in ethanol, and insoluble in chloroform and ether.

The empirical formula is C6H18N4•2HCl with a molecular weight of 219.2. The structural formula is:

NH2(CH2)2NH(CH2)2NH(CH2)2NH2•2HCI

Trientine hydrochloride is a chelating compound for removal of excess copper from the body. Syprine (trientine hydrochloride) is available as 250 mg capsules for oral administration. Syprine capsules contain gelatin, iron oxides, stearic acid, and titanium dioxide as inactive ingredients.

CLINICAL PHARMACOLOGY

Introduction

Wilson’s disease (hepatolenticular degeneration) is an autosomal inherited metabolic defect resulting in an inability to maintain a near-zero balance of copper. Excess copper accumulates possibly because the liver lacks the mechanism to excrete free copper into the bile. Hepatocytes store excess copper but when their capacity is exceeded copper is released into the blood and is taken up into extrahepatic sites. This condition is treated with a low copper diet and the use of chelating agents that bind copper to facilitate its excretion from the body.

Clinical Summary

Forty-one patients (18 male and 23 female) between the ages of 6 and 54 with a diagnosis of Wilson’s disease and who were intolerant of d-penicillamine were treated in two separate studies with trientine hydrochloride. The dosage varied from 450 to 2400 mg per day. The average dosage required to achieve an optimal clinical response varied between 1000 mg and 2000 mg per day. The mean duration of trientine hydrochloride therapy was 48.7 months (range 2-164 months). Thirty-four of the 41 patients improved, 4 had no change in clinical global response, 2 were lost to follow-up and one showed deterioration in clinical condition. One of the patients who improved while on therapy with trientine hydrochloride experienced a recurrence of the symptoms of systemic lupus erythematosus which had appeared originally during therapy with penicillamine. Therapy with trientine hydrochloride was discontinued. No other adverse reactions, except iron deficiency, were noted among any of these 41 patients.

One investigator treated 13 patients with trientine hydrochloride following their development of intolerance to d-penicillamine. Retrospectively, he compared these patients to an additional group of 12 patients with Wilson’s disease who were both tolerant of and controlled with d-penicillamine therapy, but who failed to continue any copper chelation therapy. The mean age at onset of disease of the latter group was 12 years as compared to 21 years for the former group. The trientine hydrochloride group received d-penicillamine for an average of 4 years as compared to an average of 10 years for the non-treated group.

Various laboratory parameters showed changes in favor of the patients treated with trientine hydrochloride. Free and total serum copper, SGOT and serum bilirubin all showed mean increases over baseline in the untreated group which were significantly larger than with the patients treated with trientine hydrochloride. In the 13 patients treated with trientine hydrochloride, previous symptoms and signs relating to d-penicillamine intolerance disappeared in 8 patients, improved in 4 patients, and remained unchanged in one patient. The neurological status in the trientine hydrochloride group was unchanged or improved over baseline, whereas in the untreated group, 6 patients remained unchanged and 6 worsened. Kayser-Fleischer rings improved significantly during trientine hydrochloride treatment.

The clinical outcome of the two groups also differed markedly. Of the 13 patients on therapy with trientine hydrochloride (mean duration of therapy 4.1 years; range 1 to 13 years), all were alive at the data cutoff date, and in the non-treated group (mean years with no therapy 2.7 years; range 3 months to 9 years), 9 of the 12 died of hepatic disease.

Chelating Properties

Preclinical Studies

Studies in animals have shown that trientine hydrochloride has cupriuretic activities in both normal and copper-loaded rats. In general, the effects of trientine hydrochloride on urinary copper excretion are similar to those of equimolar doses of penicillamine, although in one study they were significantly smaller.

Human Studies

Renal clearance studies were carried out with penicillamine and trientine hydrochloride on separate occasions in selected patients treated with penicillamine for at least one year. Six-hour excretion rates of copper were determined off treatment and after a single dose of 500 mg of penicillamine or 1.2 g of trientine hydrochloride. The mean urinary excretion rates of copper were as follows:

No. of Patients | Single Dose Treatment | Basal Excretion Rate (mcg Cu + + /6hr) | Test-dose Excretion Rate (mcg Cu + + /6hr)
6 | Trientine, 1.2 g | 19 | 234
4 | Penicillamine, 500 mg | 17 | 320

In patients not previously treated with chelating agents, a similar comparison was made:

No. of Patients | Single Dose Treatment | Basal Excretion Rate (mcg Cu + + /6hr) | Test-dose Excretion Rate (mcg Cu + + /6hr)
8 | Trientine, 1.2 g | 71 | 1326
7 | Penicillamine, 500 mg | 68 | 1074

These results demonstrate that Syprine is effective as a cupriuretic agent in patients with Wilson’s disease although on a molar basis it appears to be less potent or less effective than penicillamine. Evidence from a radio-labelled copper study indicates that the different cupriuretic effect between these two drugs could be due to a difference in selectivity of the drugs for different copper pools within the body.

Pharmacokinetics

Data on the pharmacokinetics of trientine hydrochloride are not available. Dosage adjustment recommendations are based upon clinical use of the drug (see DOSAGE AND ADMINISTRATION).

INDICATIONS AND USAGE

Syprine is indicated in the treatment of patients with Wilson’s disease who are intolerant of penicillamine. Clinical experience with Syprine is limited and alternate dosing regimens have not been well-characterized; all endpoints in determining an individual patient’s dose have not been well defined. Syprine and penicillamine cannot be considered interchangeable. Syprine should be used when continued treatment with penicillamine is no longer possible because of intolerable or life endangering side effects.

Unlike penicillamine, Syprine is not recommended in cystinuria or rheumatoid arthritis. The absence of a sulfhydryl moiety renders it incapable of binding cystine and, therefore, it is of no use in cystinuria. In 15 patients with rheumatoid arthritis, Syprine was reported not to be effective in improving any clinical or biochemical parameter after 12 weeks of treatment.

Syprine is not indicated for treatment of biliary cirrhosis.

CONTRAINDICATIONS

Hypersensitivity to this product.

WARNINGS

Patient experience with trientine hydrochloride is limited (see CLINICAL PHARMACOLOGY). Patients receiving Syprine should remain under regular medical supervision throughout the period of drug administration. Patients (especially women) should be closely monitored for evidence of iron deficiency anemia.

PRECAUTIONS

General

There are no reports of hypersensitivity in patients who have been administered trientine hydrochloride for Wilson’s disease. However, there have been reports of asthma, bronchitis and dermatitis occurring after prolonged environmental exposure in workers who use trientine hydrochloride as a hardener of epoxy resins. Patients should be observed closely for signs of possible hypersensitivity.

Information for Patients

Patients should be directed to take Syprine on an empty stomach, at least one hour before meals or two hours after meals and at least one hour apart from any other drug, food, or milk. The capsules should be swallowed whole with water and should not be opened or chewed. Because of the potential for contact dermatitis, any site of exposure to the capsule contents should be washed with water promptly. For the first month of treatment, the patient should have his temperature taken nightly, and he should be asked to report any symptom such as fever or skin eruption.

Laboratory Tests

The most reliable index for monitoring treatment is the determination of free copper in the serum, which equals the difference between quantitatively determined total copper and ceruloplasmin-copper. Adequately treated patients will usually have less than 10 mcg free copper/dL of serum.

Therapy may be monitored with a 24-hour urinary copper analysis periodically (i.e., every 6-12 months). Urine must be collected in copper-free glassware. Since a low copper diet should keep copper absorption down to less than one milligram a day, the patient probably will be in the desired state of negative copper balance if 0.5 to 1.0 mg of copper is present in a 24-hour collection of urine.

Drug Interactions

In general, mineral supplements should not be given since they may block the absorption of Syprine. However, iron deficiency may develop, especially in children and menstruating or pregnant women, or as a result of the low copper diet recommended for Wilson’s disease. If necessary, iron may be given in short courses, but since iron and Syprine each inhibit absorption of the other, two hours should elapse between administration of Syprine and iron.

It is important that Syprine be taken on an empty stomach, at least one hour before meals or two hours after meals and at least one hour apart from any other drug, food, or milk. This permits maximum absorption and reduces the likelihood of inactivation of the drug by metal binding in the gastrointestinal tract.

Carcinogenesis, Mutagenesis, Impairment of Fertility

Data on carcinogenesis, mutagenesis, and impairment of fertility are not available.

Pregnancy

Trientine hydrochloride was teratogenic in rats at doses similar to the human dose. The frequencies of both resorptions and fetal abnormalities, including hemorrhage and edema, increased while fetal copper levels decreased when trientine hydrochloride was given in the maternal diets of rats. There are no adequate and well-controlled studies in pregnant women. Syprine should be used during pregnancy only if the potential benefit justifies the potential risk to the fetus.

Nursing Mothers

It is not known whether this drug is excreted in human milk. Because many drugs are excreted in human milk, caution should be exercised when Syprine is administered to a nursing mother.

Pediatric Use

Controlled studies of the safety and effectiveness of Syprine in pediatric patients have not been conducted. It has been used clinically in pediatric patients as young as 6 years with no reported adverse experiences.

Geriatric Use

Clinical studies of Syprine did not include sufficient numbers of subjects aged 65 and over to determine whether they respond differently from younger subjects. Other reported clinical experience is insufficient to determine differences in responses between the elderly and younger patients. In general, dose selection should be cautious, usually starting at the low end of the dosing range, reflecting the greater frequency of decreased hepatic, renal, or cardiac function, and of concomitant disease or other drug therapy.

ADVERSE REACTIONS

Clinical experience with Syprine has been limited. The following adverse reactions have been reported in a clinical study in patients with Wilson’s disease who were on therapy with trientine hydrochloride: iron deficiency, systemic lupus erythematosus (see CLINICAL PHARMACOLOGY). In addition, the following adverse reactions have been reported in marketed use: dystonia, muscular spasm, myasthenia gravis.

Syprine is not indicated for treatment of biliary cirrhosis, but in one study of 4 patients treated with trientine hydrochloride for primary biliary cirrhosis, the following adverse reactions were reported: heartburn; epigastric pain and tenderness; thickening, fissuring and flaking of the skin; hypochromic microcytic anemia; acute gastritis; aphthoid ulcers; abdominal pain; melena; anorexia; malaise; cramps; muscle pain; weakness; rhabdomyolysis. A causal relationship of these reactions to drug therapy could not be rejected or established.

To report SUSPECTED ADVERSE REACTIONS, contact Bausch Health US, LLC at 1-800-321-4576 or FDA at 1-800-FDA-1088 or www.fda.gov/medwatch.

OVERDOSAGE

There is a report of an adult woman who ingested 30 grams of trientine hydrochloride without apparent ill effects. No other data on overdosage are available.

DOSAGE AND ADMINISTRATION

Systemic evaluation of dose and/or interval between dose has not been done. However, on limited clinical experience, the recommended initial dose of Syprine is 500-750 mg/day for pediatric patients and 750-1250 mg/day for adults given in divided doses two, three or four times daily. This may be increased to a maximum of 2000 mg/day for adults or 1500 mg/day for pediatric patients age 12 or under.

The daily dose of Syprine should be increased only when the clinical response is not adequate or the concentration of free serum copper is persistently above 20 mcg/dL. Optimal long-term maintenance dosage should be determined at 6-to 12-month intervals (see PRECAUTIONS, Laboratory Tests).

It is important that Syprine be given on an empty stomach, at least one hour before meals or two hours after meals and at least one hour apart from any other drug, food, or milk. The capsules should be swallowed whole with water and should not be opened or chewed.

HOW SUPPLIED

Syprine capsules, 250 mg, are hard gelatin capsules with light brown opaque cap and body, imprinted with “SYPRINE” on cap and “ATON/710” on the body. They are supplied as follows:

NDC 0187-2120-10 in bottles of 100.

STORAGE

Keep container tightly closed.

Store at 2° to 8°C (36° to 46°F).

Distributed by:
Bausch Health US, LLC
Bridgewater, NJ 08807 USA

Manufactured by:
Bausch Health Companies Inc.
Steinbach, MB R5G 1Z7, Canada

SYPRINE is a trademark of Bausch Health Companies Inc. or its affiliates.

© 2020 Bausch Health Companies Inc. or its affiliates

9407802-20002989
Rev. 09/2020

PRINCIPAL DISPLAY PANEL - 250 mg Capsule Carton

NDC 0187-2120-10

Rx only

SYPRINE®
(trientine hydrochloride)
Capsules

100 Capsules

250 mg

BAUSCH HEALTH